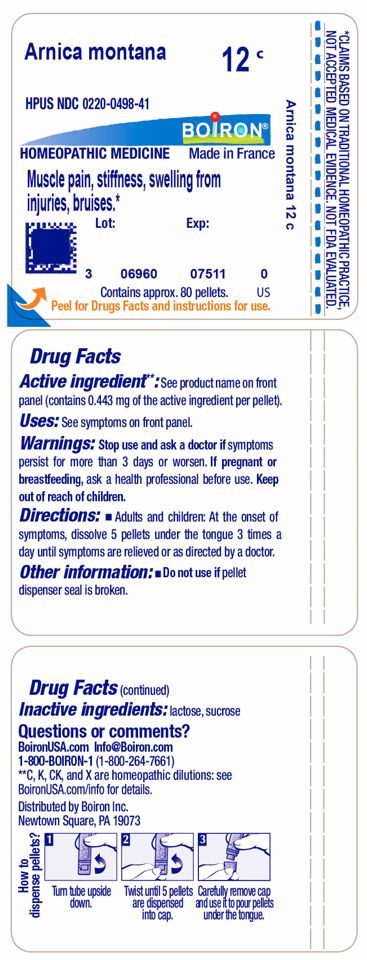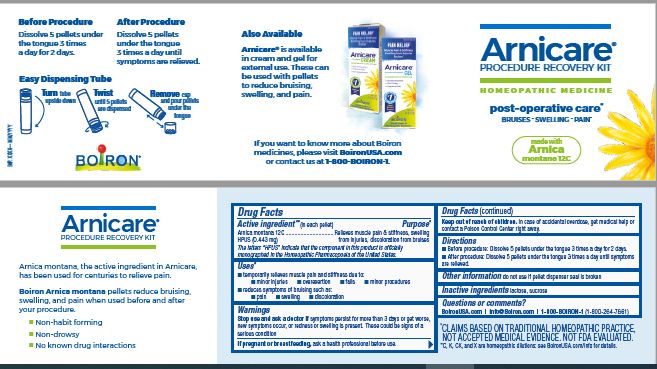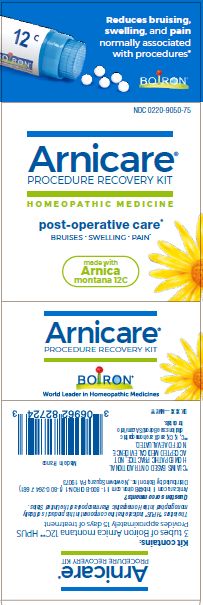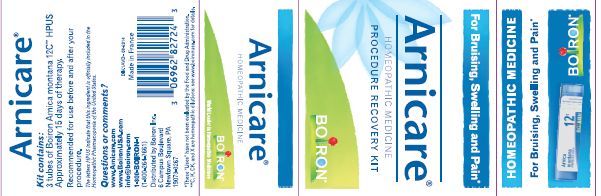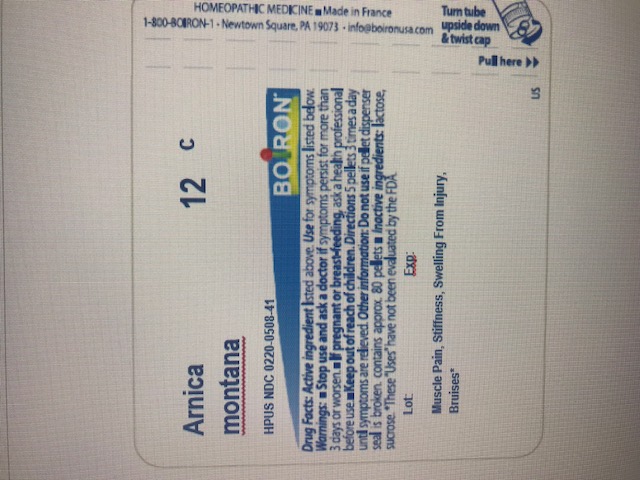 DRUG LABEL: Arnicare Procedure Recovery
NDC: 0220-9050 | Form: KIT | Route: ORAL
Manufacturer: Laboratoires Boiron
Category: homeopathic | Type: HUMAN OTC DRUG LABEL
Date: 20230105

ACTIVE INGREDIENTS: ARNICA MONTANA 30 [hp_C]/1 1
INACTIVE INGREDIENTS: SUCROSE; LACTOSE

Arnicare Procedure Recovery Kit

Active ingredient** (in each pellet)

Arnica montana 12C (0.443 mg)

The letters "HPUS" indicate that the component in this product is officially monographed in the Homeopathic Pharmacopoeia of the United States.

Purpose*

Relieves muscle pain & stiffness, swelling from injuries, discoloration from bruises

Uses*

temporarily relieves muscle pain and stiffness due to:

- minor injuries
- overexertion
- falls
- minor procedures

reduces symptoms of bruising such as:

- pain
- swelling
- discoloration

Stop use and ask a doctor if symptoms persist for more than 3 days or get worse, new symptoms occur, or redness or swelling is present. These could be signs of a serious condition.

PREGNANCY OR BREAST FEEDING

If pregnant or breastfeeding, ask a health professional before use.

Keep out of reach of children. In case of accidental overdose, get medical help or contact a Poison Control Center right away.

Directions
Before procedure: Dissolve 5 pellets under the tongue 3 times a day for 2 days.

After procedure: Dissolve 5 pellets under the tongue 3 times a day until symptoms are relieved.

INACTIVE INGREDIENT

lactose, sucrose

Questions, Comments?
www.boironusa.com
info@boironusa.com

1-800-BOIRON-1
(1-800-264-7661)

Newtown Square, PA 19073-3267

do not use if pellet dispenser seal is broken

3 tubes of Boiron Arnica montana 12C** HPUS

Provides approximately 15 days of treatment

Made in France

Boiron Arnica montana pellets reduce bruising, swelling, and pain used before and after your procedure.

Non-habit forming

Non-drowsy

No known drug interactions

post-operative care*

Dissolve 5 pellets under the tongue 3 times a day for 2 days.

Dissolve 5 pellets under the tongue 3 times a day until symptoms are relieved.

Turn tube upside down. Twist until 5 pellets are dispensed. Remove cap and pour pellets under the tongue.

*CLAIMS BASED ON TRADITIONAL HOMEOPATHIC PRACTICE, NOT ACCEPTED MEDICAL EVIDENCE. NOT FDA EVALUATED.

*C, K, CK and X are homeopathic dilutions: see BoironUSA.com/info for details.